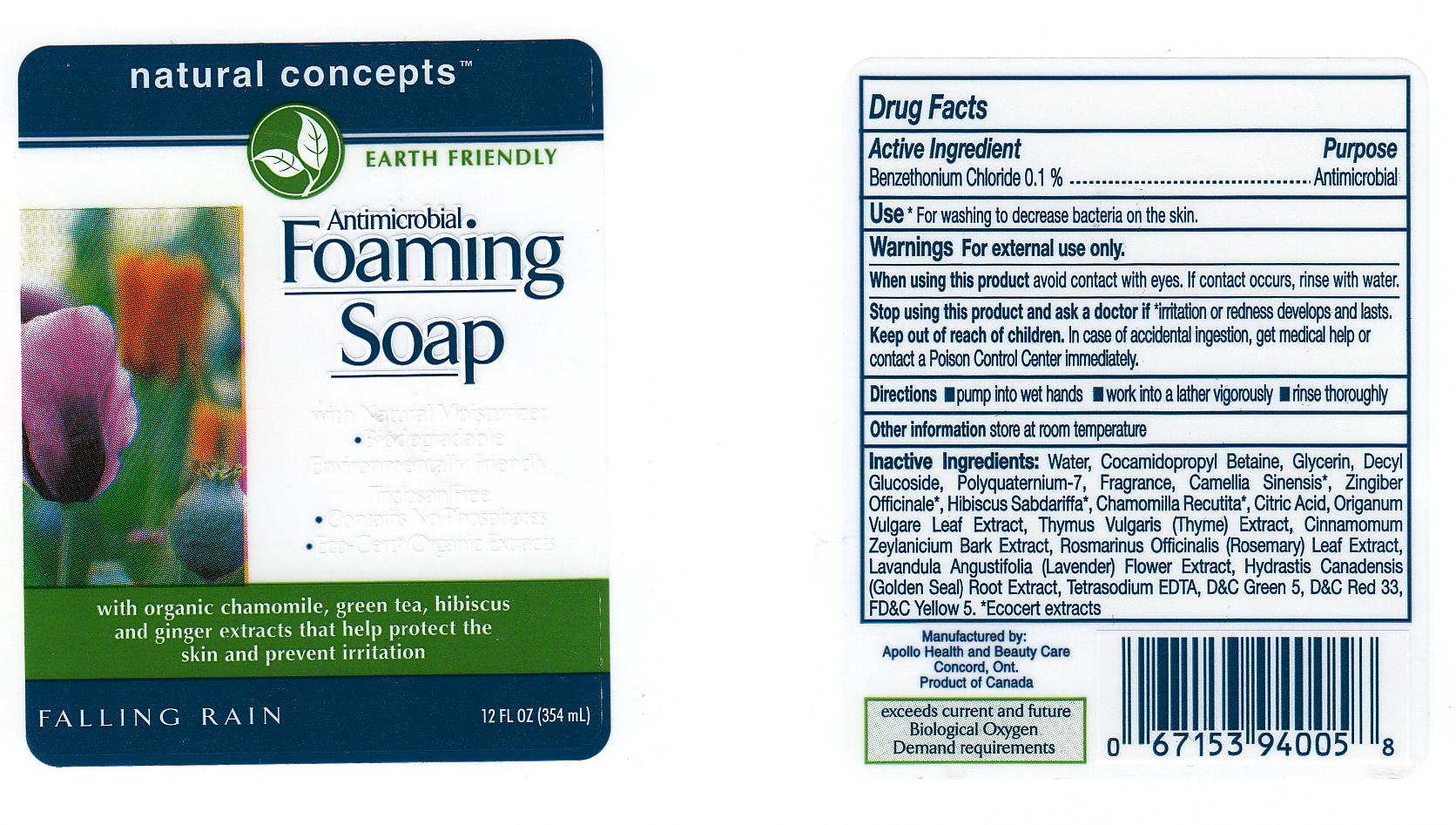 DRUG LABEL:  ANTIMICROBIAL FOAMING 
NDC: 63148-241 | Form: LIQUID
Manufacturer: APOLLO HEALTH AND BEAUTY CARE
Category: otc | Type: HUMAN OTC DRUG LABEL
Date: 20110722

ACTIVE INGREDIENTS: BENZETHONIUM CHLORIDE 0.1 mL/100 mL
INACTIVE INGREDIENTS: WATER; COCAMIDOPROPYL BETAINE; GLYCERIN; DECYL GLUCOSIDE; POLYQUATERNIUM-7 (70/30 ACRYLAMIDE/DADMAC; 1600 KD); FD&C YELLOW NO. 5; GREEN TEA LEAF; GINGER; HIBISCUS SABDARIFFA FLOWER; CHAMOMILE; CITRIC ACID MONOHYDRATE; OREGANO; THYME; CINNAMON BARK OIL; ROSEMARY; LAVANDULA ANGUSTIFOLIA FLOWER; GOLDENSEAL; EDETATE SODIUM; D&C GREEN NO. 5; D&C RED NO. 33

DRUG FACTS

ACTIVE INGREDIENT

BENZETHONIUM CHLORIDE 0.1 PERCENT

PURPOSE

ANTIMICROBIAL

USES

FOR WASHING TO DECREASE BACTERIA ON THE SKIN.

WARNINGS

FOR EXTERNAL USE ONLY.

KEEP OUT OF REACH OF CHILDREN

IN CASE OF ACCIDENTAL INGESTION, GET MEDICAL HELP OR CONTACT A POISON CONTROL CENTER IMMEDIATELY.

WHEN USING THIS PRODUCT

AVOID CONTACT WITH EYES. IF CONTACT OCCURS, RINSE WITH WATER.

STOP USING THIS PRODUCT AND ASK A DOCTOR

IF IRRITATION OR REDNESS DEVELOPS AND LASTS.

DIRECTIONS

PUMP INTO WET HANDS. WORK INTO A LATHER VIGOROUSLY. RINSE THOROUGHLY.

INACTIVE INGREDIENTS

WATER, COCAMIDOPROPYL BETAINE, GLYCERIN, DECYL GLUCOSIDE, POLYQUATERNIUM-7, FRAGRANCE, CAMELLIA SINENSIS, ZINGIBER OFFICINALE, HIBISCUS SABDARIFFA, CHAMOMILA RECUTITA, CITRIC ACID, ORIGANUM VULGARE LEAF EXTRACT, THYMUS VULGARE (THYME) EXTRACT, CINNAMOMUM ZEYLANICUM BARK EXTRACT, ROSEMARINUS OFFICINALIS (ROSEMARY) LEAF EXTRACT, LAVANDULA ANGUSTIFOLIA (LAVENDER) FLOWER EXTRACT, HYDRASTIS CANADENSIS (GOLDEN SEAL) ROOT EXTRACT, TETRASODIUM EDTA, GREEN 5, RED 33, YELLOW 5.